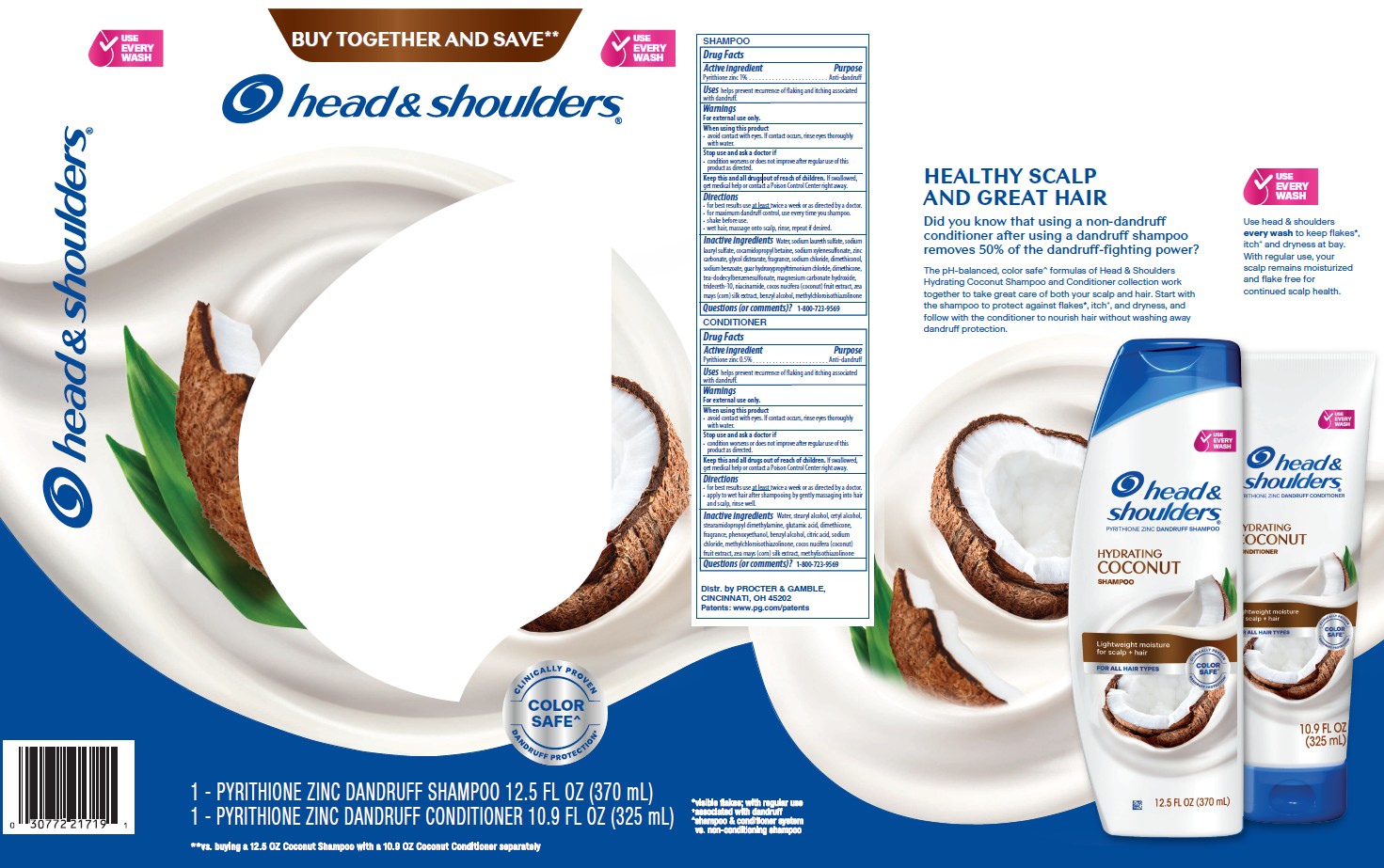 DRUG LABEL: Head and Shoulders Hydrating Coconut Kit
NDC: 84126-222 | Form: KIT | Route: TOPICAL
Manufacturer: The Procter & Gamble Manufacturing Company
Category: otc | Type: HUMAN OTC DRUG LABEL
Date: 20260219

ACTIVE INGREDIENTS: PYRITHIONE ZINC 1 g/100 mL; PYRITHIONE ZINC 0.5 g/100 mL
INACTIVE INGREDIENTS: TEA-DODECYLBENZENESULFONATE; TRIDECETH-10; NIACINAMIDE; MAGNESIUM CARBONATE HYDROXIDE; SODIUM LAURYL SULFATE; METHYLCHLOROISOTHIAZOLINONE; WATER; SODIUM LAURETH SULFATE; GLYCOL DISTEARATE; ZINC CARBONATE; SODIUM CHLORIDE; SODIUM XYLENESULFONATE; COCAMIDOPROPYL BETAINE; DIMETHICONE; SODIUM BENZOATE; COCONUT; CORN SILK; GUAR HYDROXYPROPYLTRIMONIUM CHLORIDE (1.7 SUBSTITUENTS PER SACCHARIDE); DIMETHICONOL (50000 CST); CETYL ALCOHOL; BENZYL ALCOHOL; STEARYL ALCOHOL; WATER; CETYL ALCOHOL; STEARAMIDOPROPYL DIMETHYLAMINE; GLUTAMIC ACID; PHENOXYETHANOL; BENZYL ALCOHOL; SODIUM CHLORIDE; METHYLISOTHIAZOLINONE; DIMETHICONE; CITRIC ACID; METHYLCHLOROISOTHIAZOLINONE; COCONUT; CORN SILK

Head and Shoulders Hydrating Coconut Kit

head & shoulders
SHAMPOO

Drug Facts

Active ingredient

Pyrithione zinc 1%

Purpose

Anti-dandruff

Uses

helps prevent recurrence of flaking and itching associated with dandruff.

Warnings

For external use only.

When using this product

- avoid contact with eyes. If contact occurs, rinse eyes thoroughly with water.

Stop use and ask a doctor if

- condition worsens or does not improve after regular use of this product as directed.

KEEP OUT OF REACH OF CHILDREN

Keep this and all drugs out of reach of children.

If swallowed, get medical help or contact a Poison Control Center right away.

Directions

- for best results use at least twice a week or as directed by a doctor.
- for maximum dandruff control, use every time you shampoo.
- shake before use.
- wet hair, massage onto scalp, rinse, repeat if desired.

Inactive ingredients

Water, sodium laureth sulfate, sodium lauryl sulfate, cocamidopropyl betaine, sodium xylenesulfonate, zinc carbonate, glycol distearate, fragrance, sodium chloride, dimethiconol, sodium benzoate, guar hydroxypropyltrimonium chloride, dimethicone, tea-dodecylbenzenesulfonate, magnesium carbonate hydroxide, trideceth-10, niacinamide, cocos nucifera (coconut) fruit extract, zea mays (corn) silk extract, benzyl alcohol, methylchloroisothiazolinone

Questions (or comments)?

1-800-723-9569

head & shoulders
CONDITIONER

Drug Facts

Active ingredient

Pyrithione zinc 0.5%

Purpose

Anti-dandruff

Uses

helps prevent recurrence of flaking and itching associated with dandruff.

Warnings

For external use only.

When using this product

- avoid contact with eyes. If contact occurs, rinse eyes thoroughly with water.

Stop use and ask a doctor if

- condition worsens or does not improve after regular use of this product as directed.

KEEP OUT OF REACH OF CHILDREN

Keep this and all drugs out of reach of children.

If swallowed, get medical help or contact a Poison Control Center right away.

Directions

- for best results use at least twice a week or as directed by a doctor.
- apply to wet hair after shampooing by gently massaging into hair and scalp, rinse well.

Inactive ingredients

Water, stearyl alcohol, cetyl alcohol, stearamidopropyl dimethylamine, glutamic acid, dimethicone, fragrance, phenoxyethanol, benzyl alcohol, citric acid, sodium chloride, methylchloroisothiazolinone, cocos nucifera (coconut) fruit extract, zea mays (corn) silk extract, methylisothiazolinone

Questions (or comments)?

1-800-723-9569

Dist. by PROCTER & GAMBLE,
CINCINNATI, OH 45202

PRINCIPAL DISPLAY PANEL - Kit Carton

head & shoulders

pyrithione zinc dandruff shampoo

HYDRATING COCONUT

SHAMPOO

head & shoulders

pyrithione zinc dandruff conditioner

HYDRATING COCONUT

CONDITIONER

1 PYRITHIONE ZINC DANDRUFF SHAMPOO 12.5 FL OZ (370 mL)

1 PYRITHIONE ZINC DANDRUFF CONDITIONER 10.9 FL OZ (325 mL)